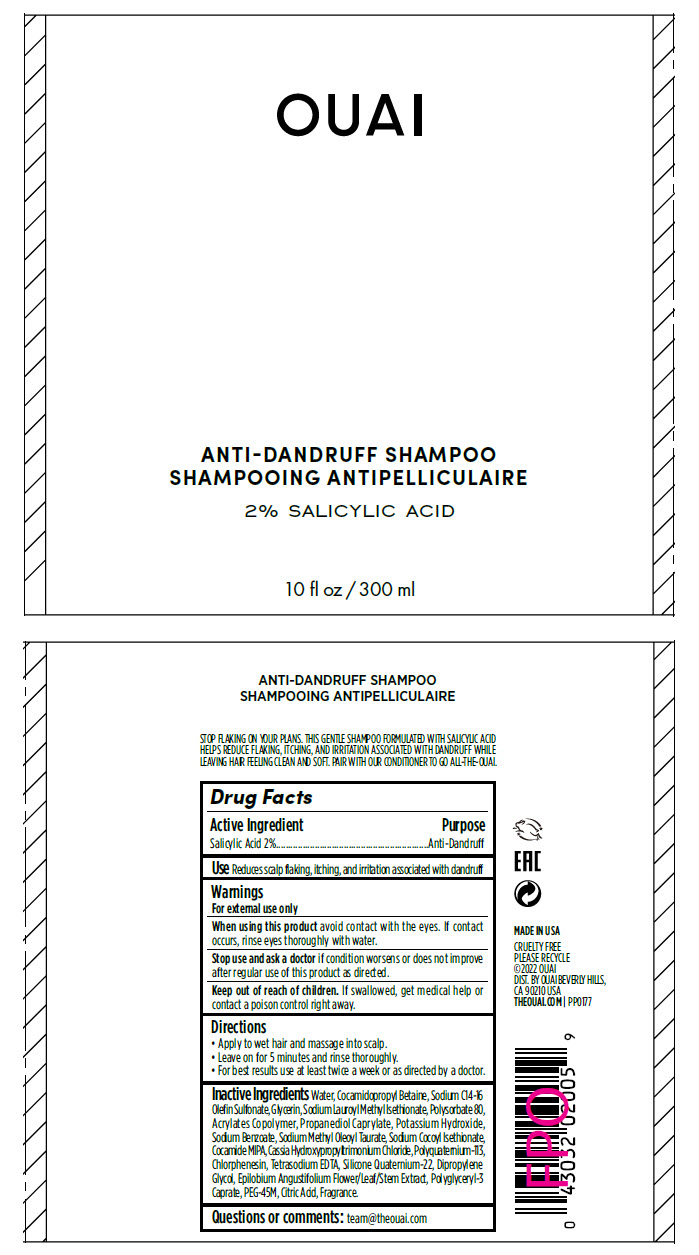 DRUG LABEL: Ouai Anti-Dandruff
NDC: 83058-0140 | Form: SHAMPOO
Manufacturer: United Beauty Brands, LLC
Category: otc | Type: HUMAN OTC DRUG LABEL
Date: 20240111

ACTIVE INGREDIENTS: Salicylic Acid 2 mg/100 mL
INACTIVE INGREDIENTS: water; Cocamidopropyl Betaine; Sodium C14-16 Olefin Sulfonate; Glycerin; Sodium Lauroyl Methyl Isethionate; Polysorbate 80; Acrylates Crosspolymer-4; Propanediol Caprylate; Potassium Hydroxide; Sodium Benzoate; Sodium Methyl Oleoyl Taurate; Sodium Cocoyl Isethionate; COCO MONOISOPROPANOLAMIDE; Chlorphenesin; EDETATE SODIUM; Dipropylene Glycol; EPILOBIUM ANGUSTIFOLIUM FLOWERING TOP; Polyglyceryl-3 Caprate; POLYETHYLENE OXIDE 2000000; CITRIC ACID MONOHYDRATE

Ouai Anti-Dandruff Shampoo

Drug Facts

Active Ingredient

Salicylic Acid 2%

Purpose

Anti-Dandruff

Use

Reduces scalp flaking, itching, and irritation associated with dandruff

Warnings

For external use only

When using this product avoid contact with the eyes. If contact occurs, rinse eyes thoroughly with water.

Stop use and ask a doctor if condition worsens or does not improve after regular use of this product as directed.

Keep out of reach of children. If swallowed, get medical help or contact a poison control right away.

Directions

- Apply to wet hair and massage into scalp.
- Leave on for 5 minutes and rinse thoroughly.
- For best results use at least twice a week or as directed by a doctor.

Inactive Ingredients

Water, Cocamidopropyl Betaine, Sodium C14-16 Olefin Sulfonate, Glycerin, Sodium Lauroyl Methyl Isethionate, Polysorbate 80, Acrylates Copolymer, Propanediol Caprylate, Potassium Hydroxide, Sodium Benzoate, Sodium Methyl Oleoyl Taurate, Sodium Cocoyl Isethionate, Cocamide MIPA, Cassia Hydroxypropyltrimonium Chloride, Polyquaternium-113, Chlorphenesin, Tetrasodium EDTA, Silicone Quaternium-22, Dipropylene Glycol, Epilobium Angustifolium Flower/Leaf/Stem Extract, Polyglyceryl-3 Caprate, PEG-45M, Citric Acid, Fragrance.

Questions or comments

team@theouai.com

DIST. BY OUAI BEVERLY HILLS,
CA 90210 USA

PRINCIPAL DISPLAY PANEL - 300 ml Bottle Label

OUAI

ANTI-DANDRUFF SHAMPOO

2% SALICYLIC ACID

10 fl oz / 300 ml